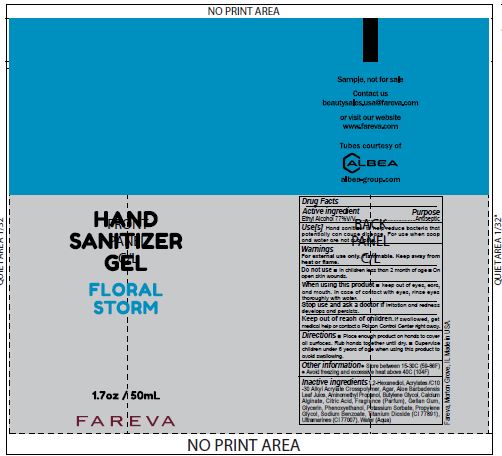 DRUG LABEL: Hand Sanitizer
NDC: 72686-184 | Form: GEL
Manufacturer: Fareva Morton Grove, Inc.
Category: otc | Type: HUMAN OTC DRUG LABEL
Date: 20201103

ACTIVE INGREDIENTS: ALCOHOL 77 mL/100 mL
INACTIVE INGREDIENTS: CARBOMER INTERPOLYMER TYPE A (55000 CPS); AMINOMETHYLPROPANOL; CITRIC ACID MONOHYDRATE; SODIUM BENZOATE; TITANIUM DIOXIDE; AGAR, UNSPECIFIED; PROPYLENE GLYCOL; POTASSIUM SORBATE; GLYCERIN; FRAGRANCE FLORAL ORC0902236; WATER; BUTYLENE GLYCOL; 1,2-HEXANEDIOL; GELLAN GUM (LOW ACYL); CALCIUM ALGINATE; PHENOXYETHANOL; ALOE VERA LEAF; ULTRAMARINE BLUE

1. Alcohol (ethanol) (USP or Food Chemical Codex (FCC) grade) (77%, volume/volume (v/v)) in an aqueous solution denatured according to Alcohol and Tobacco Tax and Trade Bureau regulations in 27 CFR part 20.
2. Glycerin
3. Fragrance
4. Sterile distilled water or boiled cold water.
5. Acrylates/C10-30 Alkyl Acrylate Crosspolymer
6. Butylene Glycol
7. Aloe Barbadensis Leaf Juice
8. Aminomethyl Propanol
9. Titanium Dioxide
10. 1,2-Hexanediol
11. Agar
12. Gellan Gum
13. Calcium Alginate
14. Ultramarines
15. Phenoxyethanol
16. Propylene Glycol
17. Citric Acid
18. Sodium Benzoate
19. Potassium Sorbate

RECENT MAJOR CHANGES

Updated to match the ingredients in our formula.

Active Ingredient(s)

Alcohol 77% v/v. Purpose: Antiseptic

Purpose

Antiseptic, Hand Sanitizer

Use

Hand Sanitizer to help reduce bacteria that potentially can cause disease. For use when soap and water are not available.

Warnings

For external use only. Flammable. Keep away from heat or flame

Do not use

- in children less than 2 months of age
- on open skin wounds

When using this product keep out of eyes, ears, and mouth. In case of contact with eyes, rinse eyes thoroughly with water.

Stop use and ask a doctor if irritation and redness develops and persists.

Keep out of reach of children. If swallowed, get medical help or contact a Poison Control Center right away.

Directions

- Place enough product on hands to cover all surfaces. Rub hands together until dry.
- Supervise children under 6 years of age when using this product to avoid swallowing.

Other information

- Store between 15-30C (59-86F)
- Avoid freezing and excessive heat above 40C (104F)

Inactive ingredients

1,2-Hexanediol, Acrylates /C10-30 Alkyl Acrylate Crosspolymer, Agar, Aloe Barbadensis Leaf Juice, Aminomethyl Propanol, Butylene Glycol, Calcium Alginate, Citric Acid, Fragrance (Parfum), Gellan Gum, Glycerin, Phenoxyethanol, Potassium Sorbate, Propylene Glycol, Sodium Benzoate, Titanium Dioxide (CI 77891), Ultramarines (CI 77007), Water (Aqua)

Package Label - Principal Display Panel

50 mL NDC: 72686-184-05